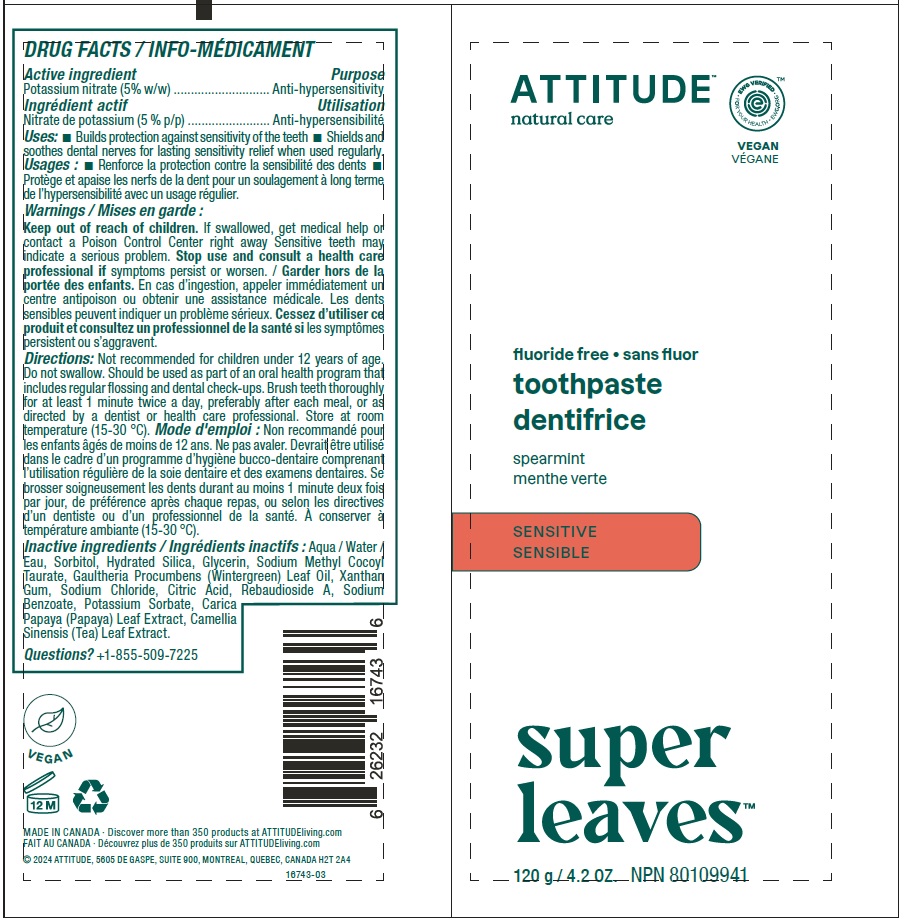 DRUG LABEL: Attitude Adult Fluoride-free - Sensitive - Spearmint
NDC: 61649-743 | Form: GEL, DENTIFRICE
Manufacturer: 9055-7588 Québec Inc. DBA Attitude
Category: otc | Type: HUMAN OTC DRUG LABEL
Date: 20240514

ACTIVE INGREDIENTS: POTASSIUM NITRATE 5 g/100 g
INACTIVE INGREDIENTS: SORBITOL; WATER; GLYCERIN; HYDRATED SILICA; SODIUM METHYL COCOYL TAURATE; METHYL SALICYLATE; XANTHAN GUM; ANHYDROUS CITRIC ACID; REBAUDIOSIDE A; SODIUM BENZOATE; CARICA PAPAYA LEAF; GREEN TEA LEAF; POTASSIUM SORBATE; SODIUM CHLORIDE

Attitude®Adult Fluoride-free Toothpaste - Sensitive - Spearmint

DRUG FACTS

Medicinal ingredient

Potassium nitrate (5% w/w)

Purpose

Anti-hypersensitivity

Uses

- Builds protection against sensitivity of the teeth.
- Shields and soothes dental nerves for lasting sensitivity relief when used regularly.

Warnings

Keep out of reach of children.

If swallowed, call a poison control centre or get medical help right away.

STOP USE

Sensitive teeth may indicate a serious problem. Stop use and consult a health care professional ifsymptoms persist or worsen.

Directions

Do not swallow. Should be used as part of an oral health program that includes regular flossing and dental check-ups. Brush teeth thoroughly for at least 1 minute twice a day, preferably after each meal, or as directed by a dentist or health care professional. Not recommended for children under 12 years of age. Store at room temperature (15-30 °C).

Non-medicinal ingredients

Aqua / Water / Eau, Sorbitol, Hydrated Silica, Glycerin, Sodium Methyl Cocoyl Taurate, Gaultheria Procumbens (Wintergreen) Leaf Oil, Xanthan Gum, Sodium Chloride, Citric Acid, Rebaudioside A, Sodium Benzoate, Potassium Sorbate, Carica Papaya (Papaya) Leaf Extract, Camellia Sinensis (Tea) Leaf Extract.

QUESTIONS?

Questions? +1-855-509-7225

PRINCIPAL DISPLAY PANEL - 120 g Tube Label

ATTITUDE®
natural care

EWG Verified

Vegan

fluoride free

toothpaste

Spearmint
SENSITIVE
Super Leaves

NPN 80109941

120 g / 4.2 OZ.